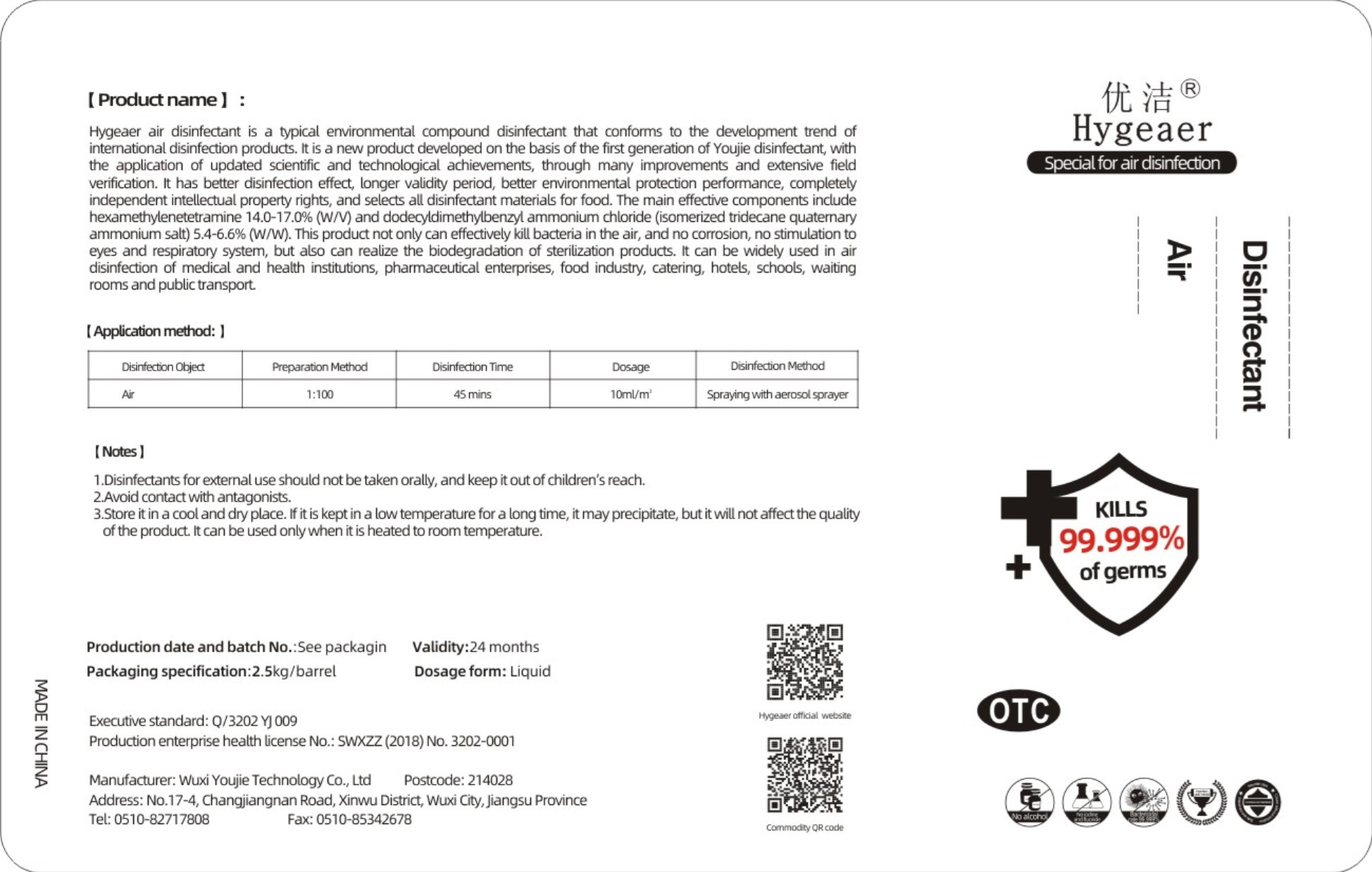 DRUG LABEL: Air Disinfectant
NDC: 54796-002 | Form: LIQUID
Manufacturer: Wuxi Youjie Technology Co. LTD
Category: otc | Type: HUMAN OTC DRUG LABEL
Date: 20200428

ACTIVE INGREDIENTS: METHENAMINE 387.5 g/2500 g; BENZALKONIUM CHLORIDE 150 g/2500 g
INACTIVE INGREDIENTS: WATER

DOSAGE AND ADMINISTRATION

Store itin a cool and dryplace.

INACTIVE INGREDIENT

water

INDICATIONS AND USAGE

Spraying with aerosolsprayer

ACTIVE INGREDIENT

METHENAMINE

BENZALKONIUM CHLORIDE

keep out of reach of children

PURPOSE

Disinfection
Sterilization

WARNINGS

1.Disinfectants for external use should not be taken orally, and keep it out of children's reach.
2.Avoid contact with antagonists.
3.Store itin a cool and dryplace. if it is kept in a lowtemperature for a long time, itmay precipitate, but itwill not afet the quality of the product It can be used onlywhen it is heated to room temperature.